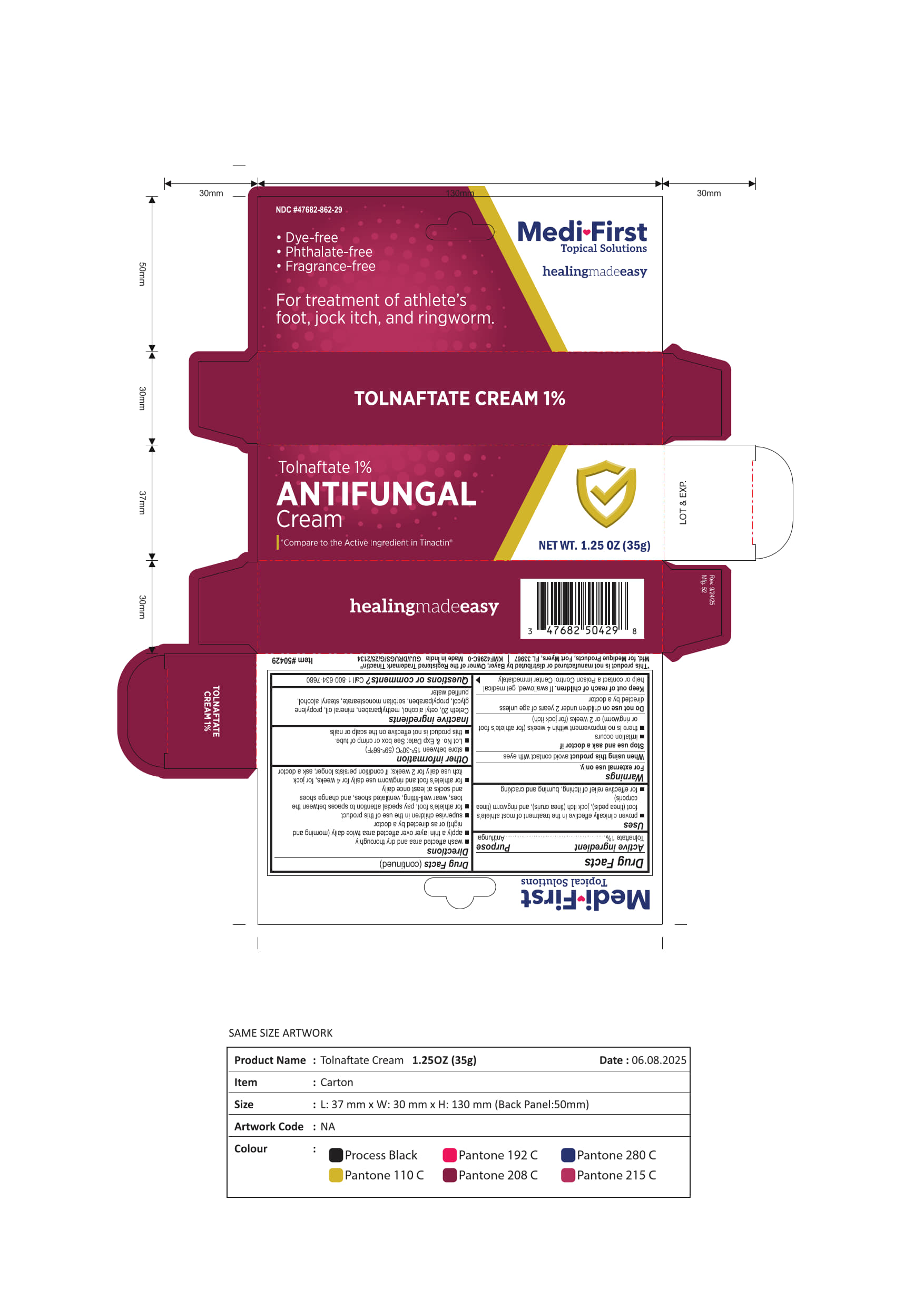 DRUG LABEL: Medi-First Tolnaftate 1% ANTIFUNGAL Cream
NDC: 47682-862 | Form: CREAM
Manufacturer: Unifirst First Aid Corporation
Category: otc | Type: HUMAN OTC DRUG LABEL
Date: 20260203

ACTIVE INGREDIENTS: TOLNAFTATE 0.1 g/1 g
INACTIVE INGREDIENTS: STEARYL ALCOHOL; PROPYLENE GLYCOL; CETETH-20; CETYL ALCOHOL; METHYLPARABEN; MINERAL OIL; PROPYLPARABEN; SORBITAN MONOSTEARATE

Medi ♥ First Tolnaftate 1% ANTIFUNGAL Cream

Drug Facts

Active Ingredient

Tolnaftate 1%

Purpose

Antifungal

Uses

- proven clinically effective in the treatment of most athletes foot (tinea pedis), job itch (tinea cruris)., and ringworm (tinea corporis)
- for effective relief of itching, burning and cracking

Warnings

For external use only.

When using this product avoid contact with eyes

Stop use and ask a doctor if

- irritation occurs
- there is no improvement within 4 weeks (for athlete's foot or ringworm) or 2 weeks (for jock itch)

Do not use on children under 2 years of age unless directed by a doctor

Keep our of reach of children

Keep out of reach of children.

If swallowed, get medical help or contact a Poison Control Center immediately.

Directions

- wash affected area and dry thoroughly
- apply a thin layer over affected area twice daily (morning and night) or as directed by a doctor
- supervise children in the use of this product
- for athlete's foot, pay special attention to spaces between the toes, wear well-fitting, ventilated shoes, and change shoes and socks at least once daily
- for athlete's foot and ringworm use daily for 4 weeks, for jock itch use daily for 2 weeks; if condition persists longer, ask a doctor

Other information

- Store between 15°-30° *(59°-86°F)
- Lot No. & Exp Date: See box or crimp of tube.
- this product is not effective on the scalp or nails

Inactive ingredients

Ceteth 20, cetyl alcohol, methylparaben, mineral oil, propylen glycol, propylparaben, sorbitan monostearate, stearyl alcohol, purified water

Questions or comments? Call 1-800-635-7680

Principal Display Panel

Medi ♥ First

Topical Solutions

healingmade easy

NDC #47682-862-29

- Dye-free
- Phthalate-free
- Fragrance-free

For treatment of athlete's

foot, jock itch, and ringworm